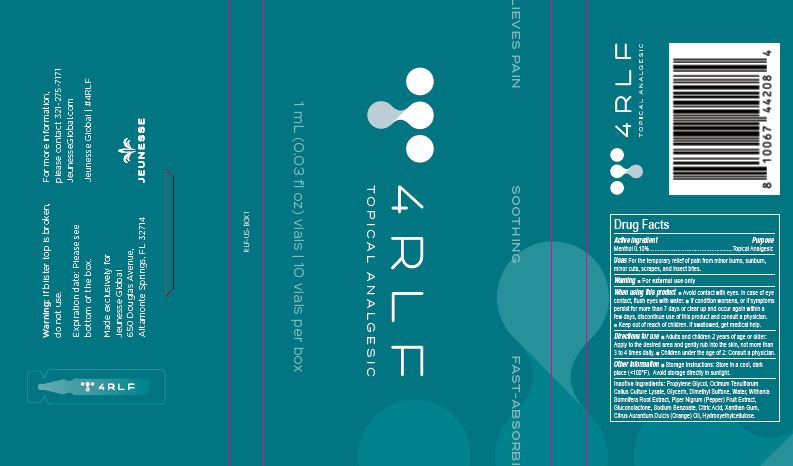 DRUG LABEL: 4RLF Topical Analgesic
NDC: 76849-201 | Form: CREAM
Manufacturer: Rinati Skin, LLC
Category: otc | Type: HUMAN OTC DRUG LABEL
Date: 20221028

ACTIVE INGREDIENTS: MENTHOL 0.1 g/1 mL
INACTIVE INGREDIENTS: PROPYLENE GLYCOL; OCIMUM TENUIFLORUM WHOLE; GLYCERIN; DIMETHYL SULFONE; WATER; WITHANIA SOMNIFERA ROOT; PIPER NIGRUM WHOLE; GLUCONOLACTONE; SODIUM BENZOATE; CITRIC ACID MONOHYDRATE; XANTHAN GUM; CITRUS AURANTIUM FRUIT OIL; CETYL HYDROXYETHYLCELLULOSE (350000 MW)

RINATI - JEUNESSE - 4RLF Topical Analgesic (76849-201)

ACTIVE INGREDIENTS

Menthol 0.10%

PURPOSE

TOPICAL ANALGESIC

USES

For the temporary relief of pain from minor burns, sunburn, minor cuts, scrapes, and insect bites.

WARNINGS

For external use only. When using this product ■ Avoid contact with eyes. In case of eye contact, flush eyes with water. ■ If condition worsens, or if symptoms persist for more than 7 days or clear up and occur again within a few days, discontinue use of this product and consult a physician.

■ Keep out of reach of children.

If swallowed, get medical help.

DIRECTIONS FOR USE

■ Adults and children 2 years of age or older:
Apply to the desired area and gently rub into the skin, not more than
3 to 4 times daily. ■ Children under the age of 2: Consult a physician.

INACTIVE INGREDIENTS

Propylene Glycol, Ocimum Tenuiflorum Callus Culture Lysate, Glycerin, Dimethyl Sulfone, Water, Withania Somnifera Root Extract, Piper Nigrum (Pepper) Fruit Extract, Gluconolactone, Sodium Benzoate, Citric Acid, Xanthan Gum, Citrus Aurantium Dulcis (Orange) Oil, Hydroxyethylcellulose.

OTHER INFORMATION

■ Storage Instructions: Store in a cool, dark place (<100°F). Avoid storage directly in sunlight.